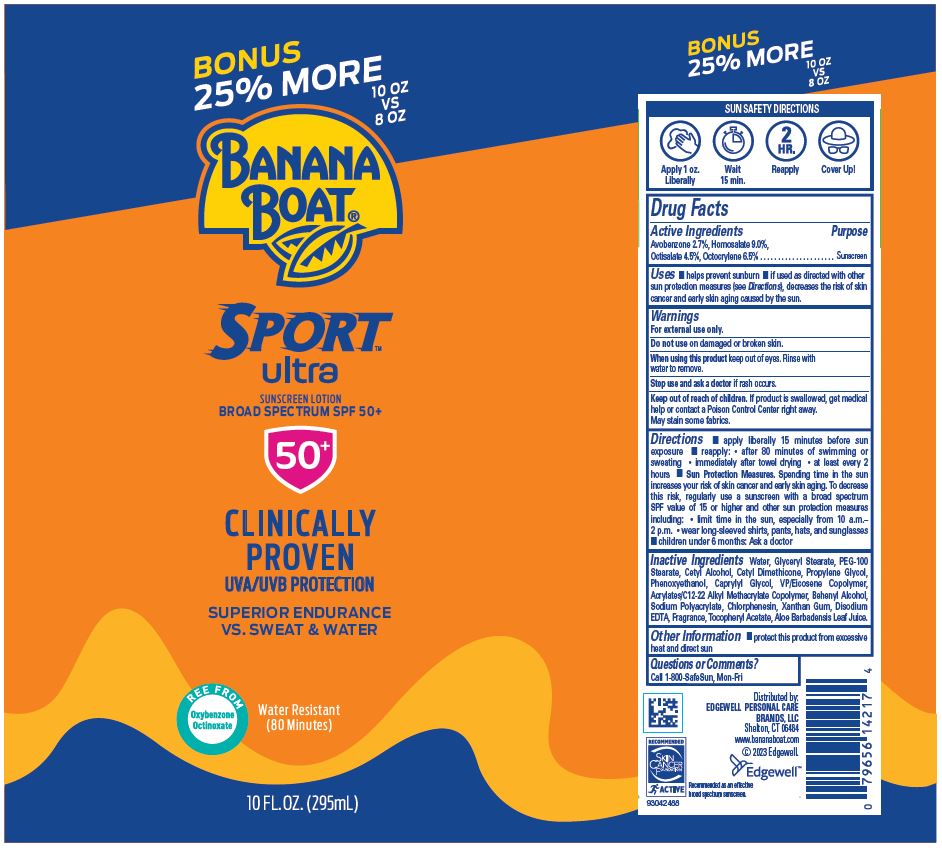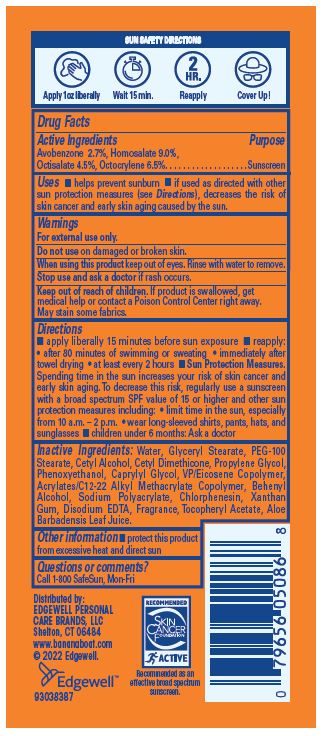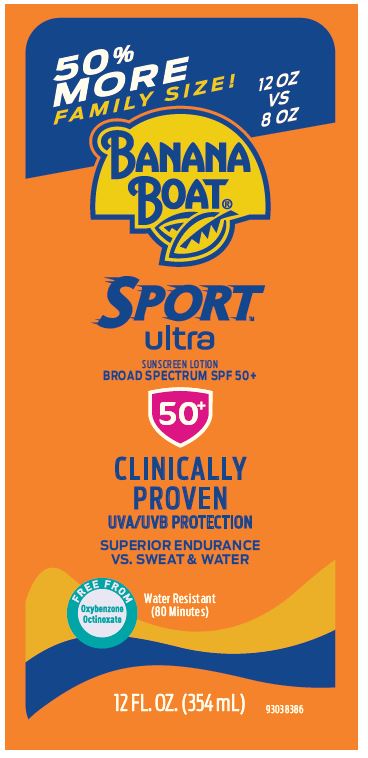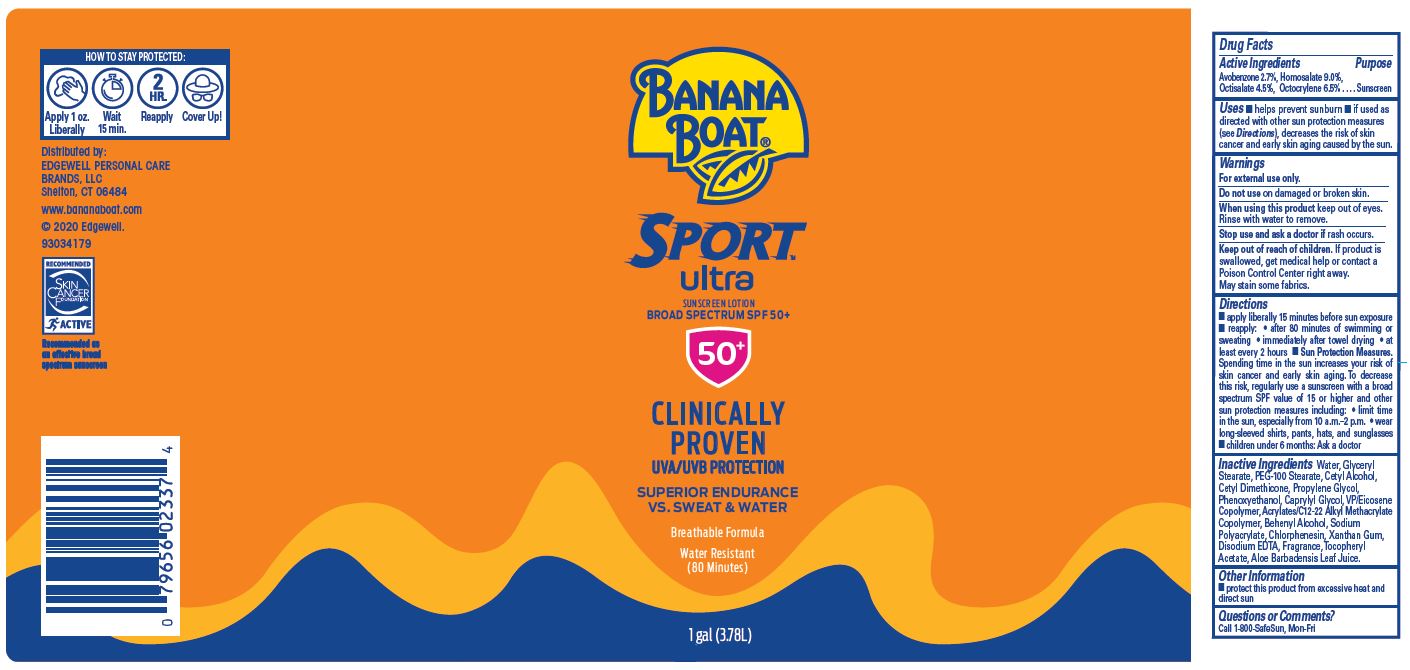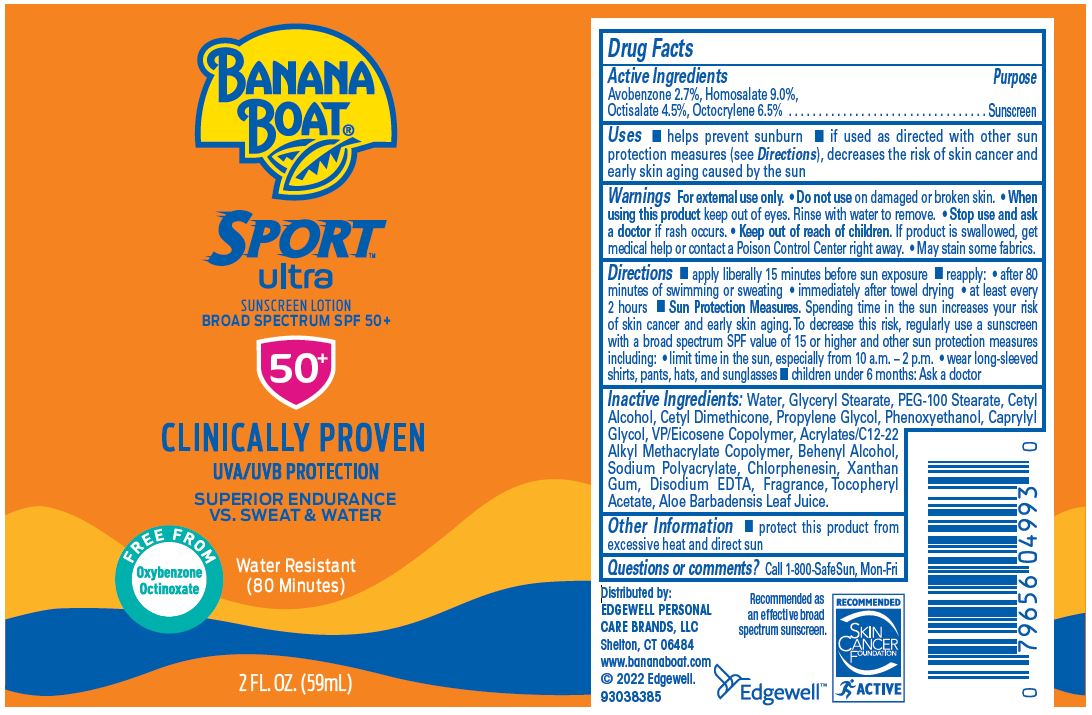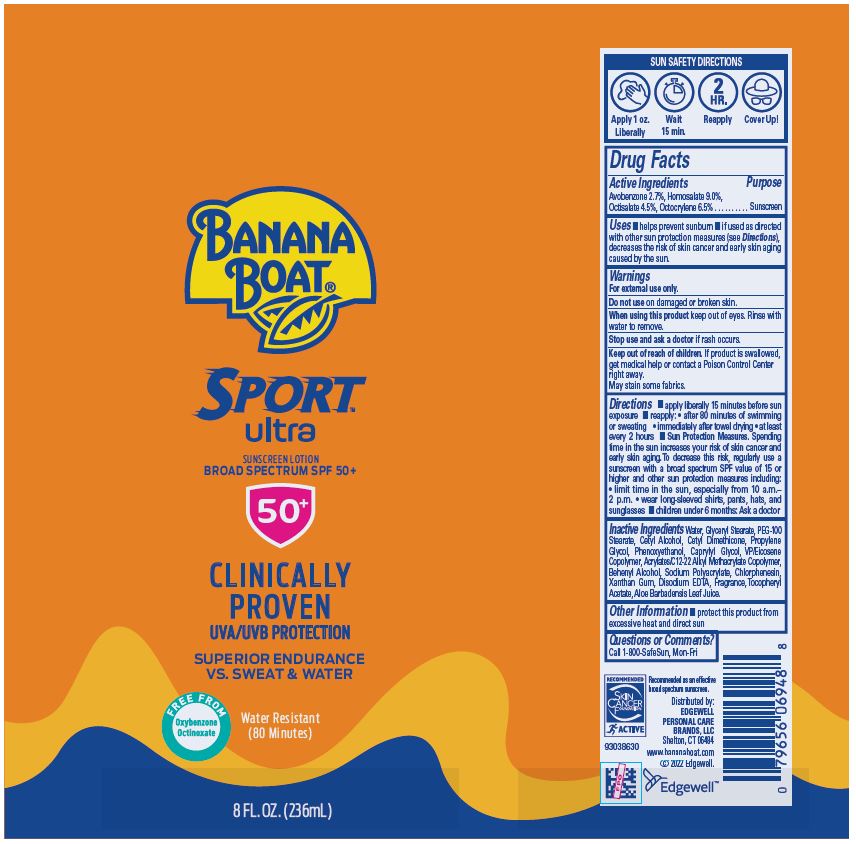 DRUG LABEL: Banana Boat Ultra Sport Sunscreen Broad Spectrum SPF 50
NDC: 63354-689 | Form: LOTION
Manufacturer: Edgewell Personal Care Brands LLC
Category: otc | Type: HUMAN OTC DRUG LABEL
Date: 20251106

ACTIVE INGREDIENTS: OCTOCRYLENE 6.5 g/100 g; AVOBENZONE 2.7 g/100 g; HOMOSALATE 9 g/100 g; OCTISALATE 4.5 g/100 g
INACTIVE INGREDIENTS: CAPRYLYL GLYCOL; CHLORPHENESIN; PHENOXYETHANOL; VINYLPYRROLIDONE/EICOSENE COPOLYMER; XANTHAN GUM; EDETATE DISODIUM ANHYDROUS; ALOE VERA LEAF; GLYCERYL MONOSTEARATE; CETYL ALCOHOL; PROPYLENE GLYCOL; DOCOSANOL; PEG-100 STEARATE; WATER; .ALPHA.-TOCOPHEROL ACETATE

Active Ingredients

Avobenzone 2.7%, Homosalate 9.0%, Octisalate 4.5%, Octocrylene 6.5%

Purpose

Sunscreen

Uses

• helps prevent sunburn • if used as directed with other sun protection measures (see Directions), decreases the risk of skin cancer and early skin aging caused by the sun

Warnings

For external use only

May stain some fabrics.

Do not use

on damaged or broken skin

When using this product

keep out of eyes. Rinse with water to remove.

Stop use and ask a doctor

if rash occurs

Keep out of reach of children

If product is swallowed, get medical help or contact a Poison Control Center right away

May stain

some fabrics

Directions

• apply liberally 15 minutes before sun exposure • reapply: • after 80 minutes of swimming or sweating • immediately after towel drying • at least every 2 hours • Sun Protection Measures. Spending time in the sun increases your risk of skin cancer and early skin aging. To decrease this risk, regularly use a sunscreen with a broad spectrum SPF of 15 or higher and other sun protection measures including: • limit time in the sun, especially from 10 a.m. - 2 p.m. • wear long-sleeved shirts, pants, hats, and sunglasses • children under 6 months: Ask a doctor

Inactive ingredients

Water, Glyceryl Stearate, PEG-100 Stearate, Cetyl Alcohol, Cetyl Dimethicone, Propylene Glycol, Phenoxyethanol, Caprylyl Glycol, VP/Eicosene Copolymer, Acrylates/C12-22 Alkyl Methacrylate Copolymer, Behenyl Alcohol, Sodium Polyacrylate, Chlorphenesin, Xanthan Gum, Disodium EDTA, Fragrance, Tocopheryl Acetate, Aloe Barbadensis Leaf Juice

Other information

• protect this product from excessive heat and direct sun

Questions or comments?

Call 1-800-SafeSun, Mon-Fri

Principal Display Panel

BANANA
BOAT®
SPORT™
ultra
SUNSCREEN LOTION
BROAD SPECTRUM SPF 50+
CLINICALLY PROVEN
UVA/UVB PROTECTION
SUPERIOR ENDURANCE
VS. SWEAT & WATER
FREE FROM
Oxybenzone
Octinoxate
Water Resistant
(80 Minutes)
2 FL. OZ. (59mL)

BANANA
BOAT®
SPORT™
ultra
SUNSCREEN LOTION
BROAD SPECTRUM SPF 50+
CLINICALLY PROVEN
UVA/UVB PROTECTION
SUPERIOR ENDURANCE
VS. SWEAT & WATER
FREE FROM
Oxybenzone
Octinoxate
Water Resistant
(80 Minutes)
8 FL. OZ. (236mL)

BONUS
25% MORE
10 OZ
VS
8 OZ
BANANA
BOAT®
SPORT™
ultra
SUNSCREEN LOTION
BROAD SPECTRUM SPF 50+
CLINICALLY PROVEN
UVA/UVB PROTECTION
SUPERIOR ENDURANCE
VS. SWEAT & WATER
FREE FROM
Oxybenzone
Octinoxate
Water Resistant
(80 Minutes)
10 FL. OZ. (295mL)

50%

MORE
FAMILY SIZE!
12 OZ
VS
8 OZ
BANANA
BOAT®
SPORT™
ultra
SUNSCREEN LOTION
BROAD SPECTRUM SPF 50+
CLINICALLY PROVEN
UVA/UVB PROTECTION
SUPERIOR ENDURANCE
VS. SWEAT & WATER
FREE FROM
Oxybenzone
Octinoxate
Water Resistant
(80 Minutes)
12 FL. OZ. (354mL)

BANANA
BOAT®
SPORT™
ultra
SUNSCREEN LOTION
BROAD SPECTRUM SPF 50+
CLINICALLY PROVEN
UVA/UVB PROTECTION
SUPERIOR ENDURANCE
VS. SWEAT & WATER
Breathable Formula
Water Resistant
(80 Minutes)
1 gal (3.78L)